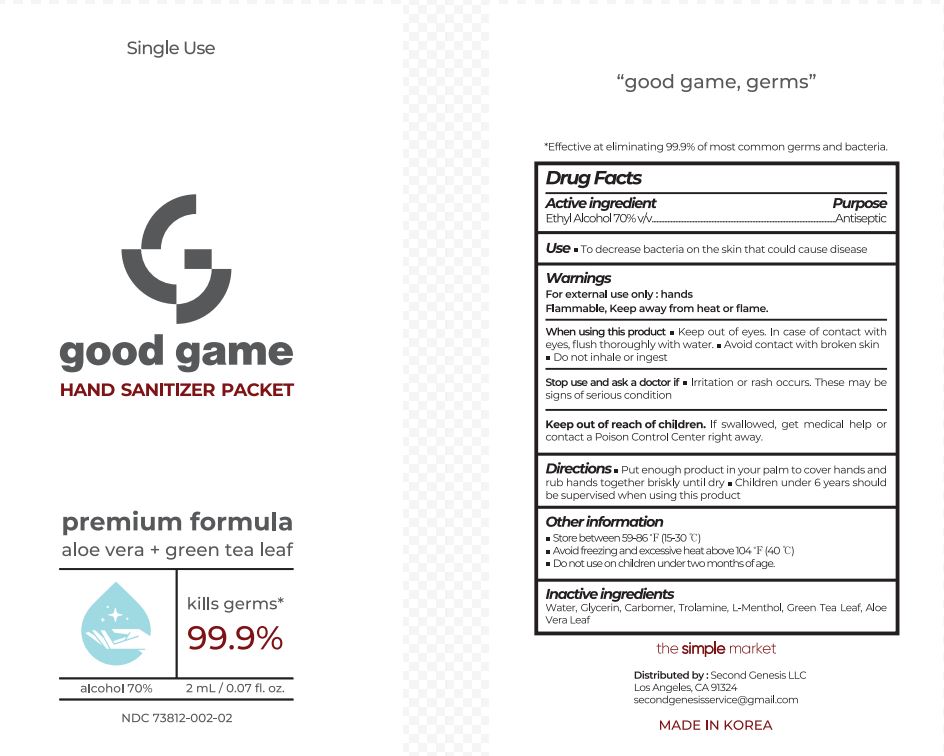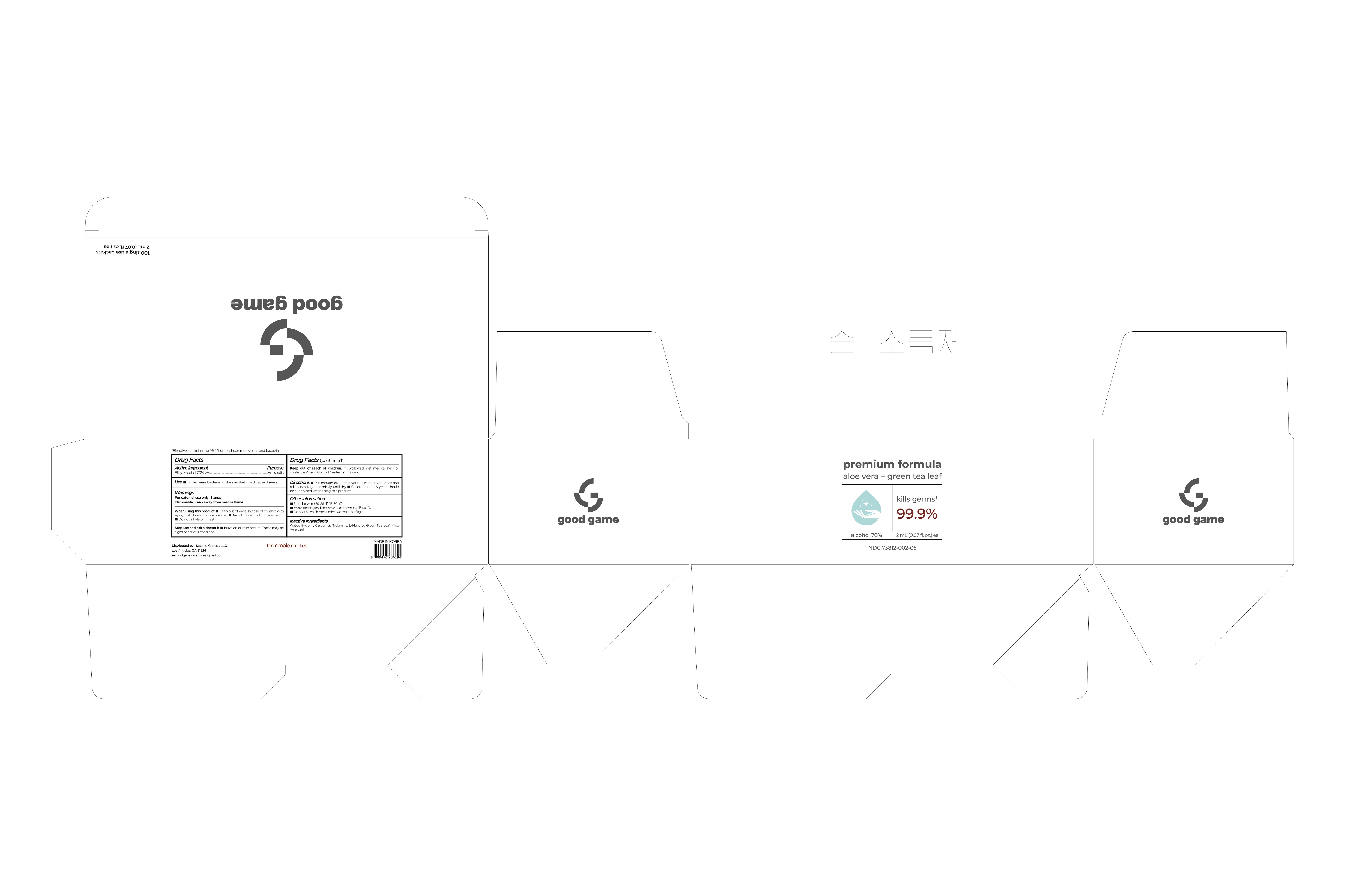 DRUG LABEL: HAND SANITIZER PREMIUM FORMULA
NDC: 73812-002 | Form: GEL
Manufacturer: LTP Global
Category: otc | Type: HUMAN OTC DRUG LABEL
Date: 20200622

ACTIVE INGREDIENTS: ALCOHOL 70 mL/100 mL
INACTIVE INGREDIENTS: ALOE VERA LEAF; TROLAMINE; LEVOMENTHOL; GLYCERIN; CARBOMER HOMOPOLYMER TYPE B (ALLYL PENTAERYTHRITOL CROSSLINKED); WATER; GREEN TEA LEAF

Active Ingredient

Ethyl Alcohol 70% v/v. Purpose: Antiseptic

Purpose

Antiseptic

Use

- to decrease bacteria on the skin that could cause disease

Warnings

For external use only : hands

Flammable. Keep away from heat or flame.

When using this product

- keep out of eyes. In case of contact with eyes, flush thoroughly with water.
- avoid contact with broken skin
- do not inhale or ingest

Stop use and ask a doctor if

- irritation or rash occurs. These may be signs of serious condition.

Keep out of reach of children. If swallowed, get medical help or contact a Poison Control Center right away.

Directions

- Put enough product in your palm to cover hands and rub hands together briskly until dry
- Children under 6 years should be supervised when using this product

Other information

- Store between 59-86°F (15-30°C)
- Avoid freezing and excessive heat above 104°F (40°C)
- Do not use on children under two months of age.

Inactive ingredients

Water, Glycerin, Carbomer, Trolamine, L-Menthol, Green Tea Leaf, Aloe Vera Leaf